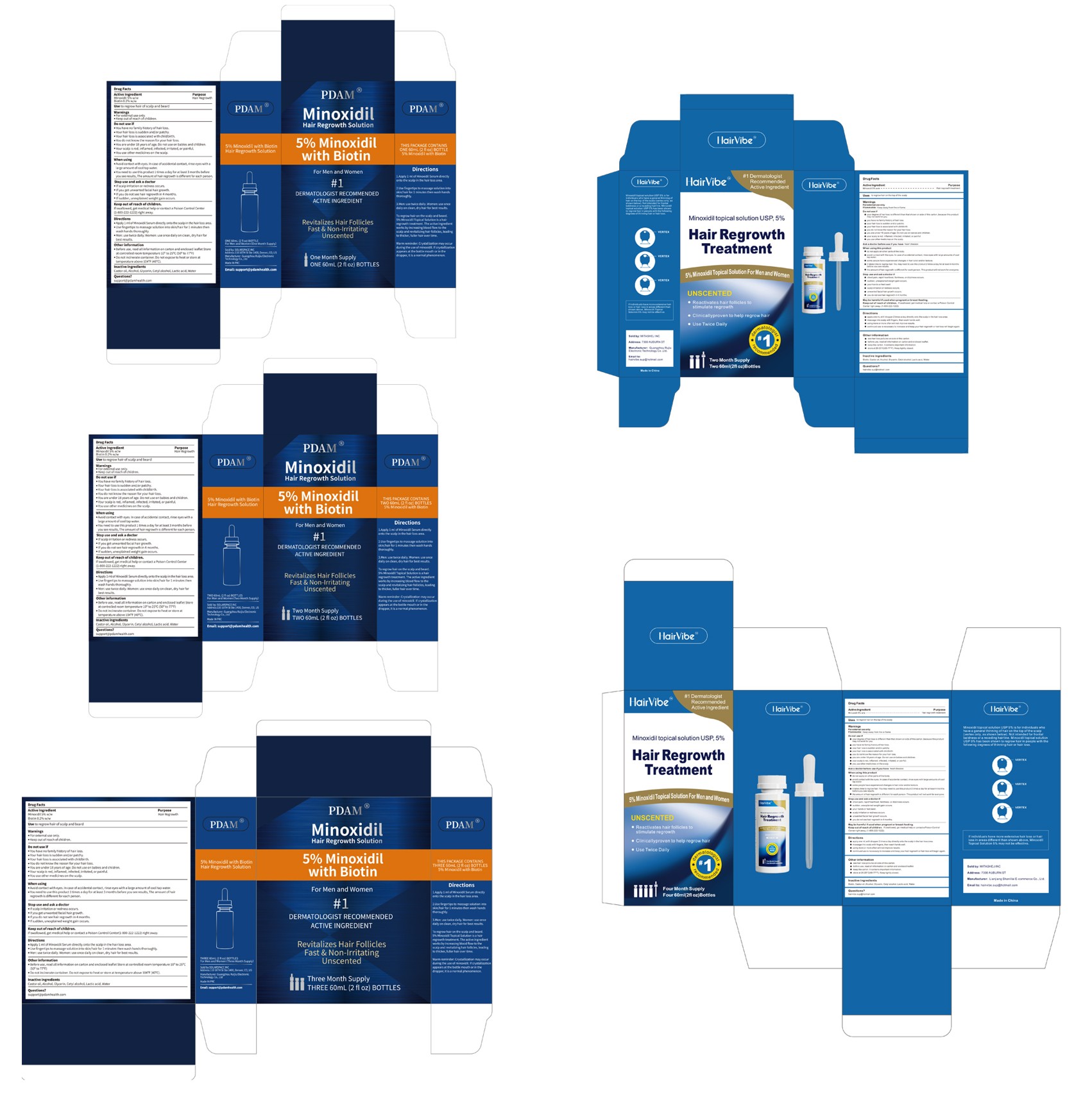 DRUG LABEL: Minoxidil Hair Regrowth Solution
NDC: 85038-007 | Form: SOLUTION
Manufacturer: Lianjiang Shanlilai E-commerce Co., Ltd.
Category: otc | Type: HUMAN OTC DRUG LABEL
Date: 20250624

ACTIVE INGREDIENTS: MINOXIDIL 5 g/100 mL
INACTIVE INGREDIENTS: GLYCERIN; CASTOR OIL; ALCOHOL; CETYL ALCOHOL; WATER; BIOTIN; LACTIC ACID

85038-007 Minoxidil Hair Regrowth Solution

ACTIVE INGREDIENT

Minoxidil 5%

PURPOSE

Hair regrowth treatment

INDICATIONS AND USAGE

Uses to regrow hair on the top of the scalp

WARNINGS

For external use only.
Flammable: Keep away from fire or flame

DO NOT USE

your degree of hair loss is different than that shown on side of this carton ,because this product may not work for you.
you have no family history of hair loss.
your hairloss is sudden and/or patchy.
your hairloss is associated with childbirth.
you do not know the reason for your hair loss.
you are under 18 years of age. Do not use on babies and children.
your scalp is red,inflamed,infected,irritated, or painful.
you use other medicines on the scalp.

WHEN USING

do not apply on other parts of the body.
avoid contact with the eyes. in case of accidental contact, rinse eyes with large amounts of cool tap water.
some people have experienced changes in hair color and/or texture
it takes time to regrow hair. You may need to use this product 2 times a day for at least 4 monthspefore you see results.
the amount of hair regrowth is diferent for each person. This product will not work for everyone

STOP USE

chest pain,rapid heartbeat,faintness, or dizziness occurs.
sudden, unexplained weight gain occurs.
your hands or feet swel.
scalp irritation or redness occurs.
unwanted facial hair growth occurs.
you do not see hair regrowth in 4 months

Keep out of reach of children. lfswallowed, get medical help or contact a Poison Control Centerright away.(1-800-222-1222)

DOSAGE AND ADMINISTRATION

apply one mL with dropper 2 times a day directly onto the scalp in the hair loss area.
massageinto scalp with fingers, then wash hands well.
using more or more often will notimprove results.
continued use is necessary to increase and keep your hair regrowth or hair loss will begin again.

INACTIVE INGREDIENT

biotin
castor oil
alcohol
glycerin
cetyl alcohol
lactic acid
water